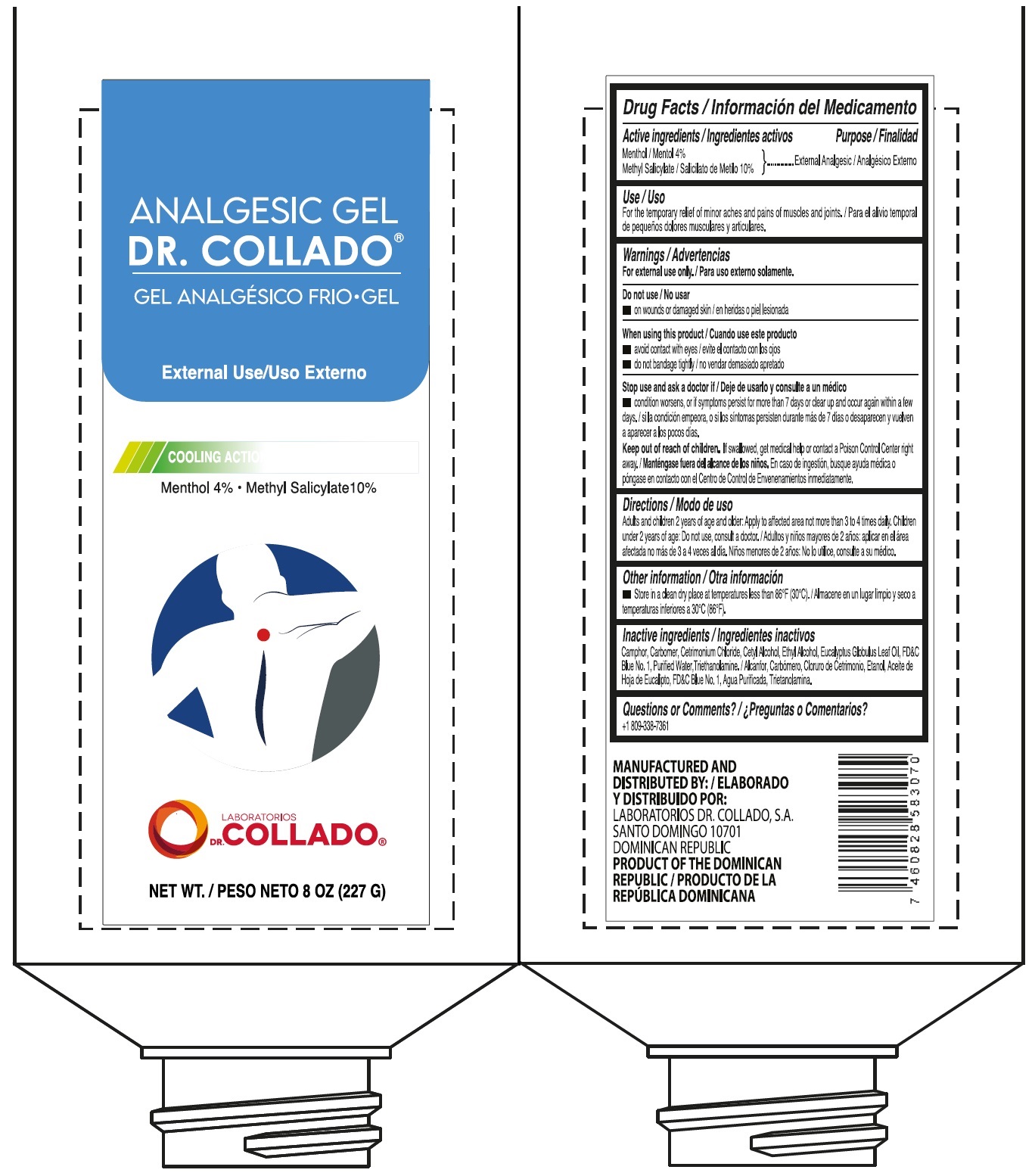 DRUG LABEL: Analgesic Gel Dr. Collado Menthol 4 Methyl Salicylate
NDC: 42333-000 | Form: OINTMENT
Manufacturer: Laboratorios Dr. Collado, S.A.
Category: otc | Type: HUMAN OTC DRUG LABEL
Date: 20260129

ACTIVE INGREDIENTS: MENTHOL 40 mg/1 g; METHYL SALICYLATE 100 mg/1 g
INACTIVE INGREDIENTS: CAMPHOR (SYNTHETIC); CARBOMER HOMOPOLYMER, UNSPECIFIED TYPE; CETRIMONIUM CHLORIDE; CETYL ALCOHOL; ALCOHOL; EUCALYPTUS OIL; FD&C BLUE NO. 1; WATER; TROLAMINE

Analgesic Gel Dr. Collado Menthol 4% Methyl Salicylate

Active ingredients

Menthol 4%Methyl Salicylate 10%

Purpose

External Analgesic

Use

For the temporary relief of minor aches and pains of muscles and joints.

Warnings

For external use only.

Do not use

- on wounds or damaged skin

When using this product

- avoid contact with eyes
- do not bandage tightly

Stop use and ask a doctor if

- condition worsens, or if symptoms persist for more than 7 days or clear up and occur again within a few days.

Keep out of reach of children.

If swallowed, get medical help or contact a Poison Control Center right away.

Directions

Audlts and children 2 years of age and older: Apply to affected area not more than 3 to 4 times daily. Children under 2 yeas of age: Do not use, consult a doctor.

Other information

- Store in a clean dry place at temperatures less than 86°F (30°C)

Inactive ingredients

Camphor, Carbomer, Cetrimonium Chloride, Cetyl Alcohol, Ethyl Alcohol, Eucalyptus Globulus Leaf Oil, FD&C Blue No.1, Purified Water, Triethanolamine.

Questions or Comments?

+1 809-338-7361